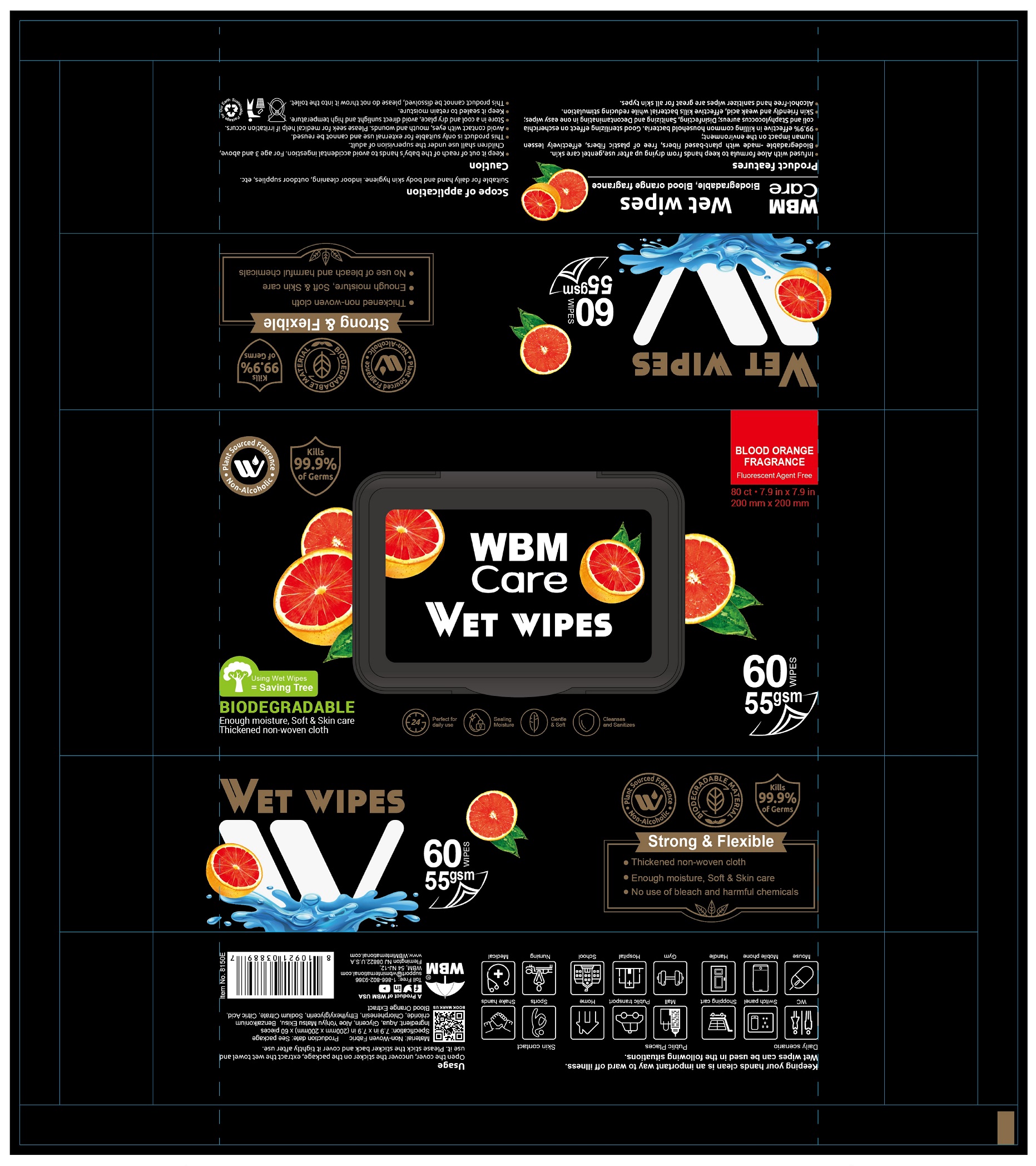 DRUG LABEL: WBM Care Wet Wipes
NDC: 78724-104 | Form: SWAB
Manufacturer: Jiebao Daily Chemical (Xiangxi)Co.,Ltd
Category: otc | Type: HUMAN OTC DRUG LABEL
Date: 20211210

ACTIVE INGREDIENTS: Benzalkonium Chloride 0.13 g/100 g
INACTIVE INGREDIENTS: water; GLYCERIN; CHLORPHENESIN; ETHYLHEXYLGLYCERIN; SODIUM CITRATE

Wet Wipes

Active Ingredient

Benzalkonium Chloride ...... 0.13%

Purpose

Antiseptic

USE

Suitable for daily hand and body skin hygiene, indoor cleaning, outdoor supplies, etc.

Open the cover, uncover the sticker on the package, extract the wet towel and use it. Please stick the sticker back and cover it tightly after use.

Warning

- Keep it out of reach of the baby's hands to avoid accidental ingestion. For age 3 and above, Children shall use under the supervision of adult.
- This product is only suitable for external use and can not be reused.
- Avoid contact with eyes, mouth and wounds. Please seek for medical help if irritation occurs.
- Store in a cool and dry place, avoid direct sunlight and high temperature.
- Keep it sealed to retain moisture.
- This product cannot be dissolved, please do not thro it into the toilet.

KEEP OUT OF REACH OF CHILDREN

●If swallowed, get medical help or contact a Poison Contrl Center right away.

Directions

- Wipe hands, fingers, interdigirtal areas and wrists throughly with towelette. Be sure to utilze the entire wipe surface. Allow to dry.

Inactive ingredients

Aqua, Glycerin, Aloe Yohijyu Matsu Ekisu, Chlorphenesin, Ethylhexyglycerin, Sodium Citrate, Citric Acid, Blook Orange Extract